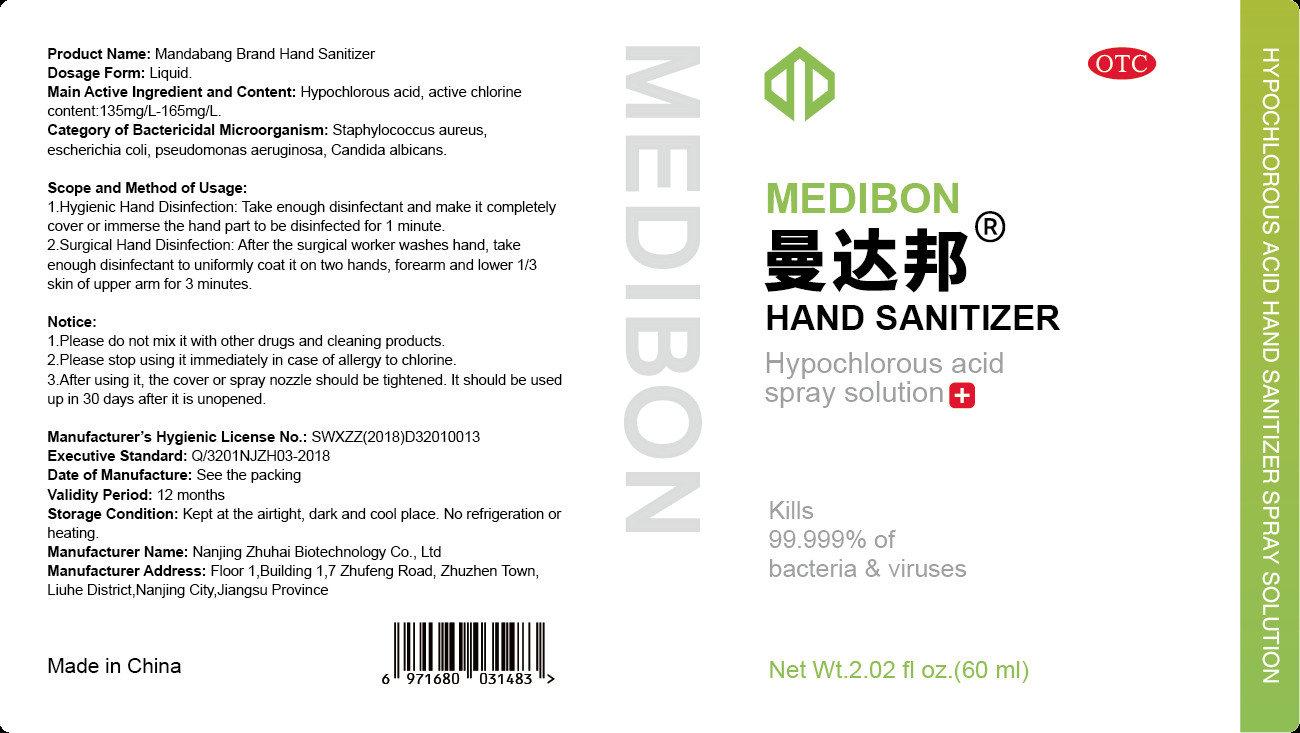 DRUG LABEL: Mandabang Brand Hand Sanitizer
NDC: 55406-001 | Form: LIQUID
Manufacturer: Nanjing Zhuhai Biotechnology Co., Ltd
Category: otc | Type: HUMAN OTC DRUG LABEL
Date: 20200511

ACTIVE INGREDIENTS: HYPOCHLOROUS ACID 9 mg/60 mL
INACTIVE INGREDIENTS: WATER

DOSAGE AND ADMINISTRATION

Kept at the airtight, dark and cool place. No refrigeration or heating.

INACTIVE INGREDIENT

WATER

INDICATIONS AND USAGE

1.Hygienic Hand Disinfection: Take enough disinfectant and make it completely cover or immerse the hand part to be disinfected for 1 minute.
2. Surgical Hand Disinfection: After the surgical worker washes hand, take enough disinfectant to uniformly coat it on two hands, forearm and lower 1/3 skin of upper arm for 3 minutes.

ACTIVE INGREDIENT

Hypochlorous acid

keep out of reach of children

PURPOSE

Disinfection
Sterilization

WARNINGS

1.Please do not mix it with other drugs and cleaning products.
2.Please stop using it immediately in case of allergy to chlorine.
3.After using it, the cover or spray nozzle should be tightened. It should be used up in 30 days after it is unopened.